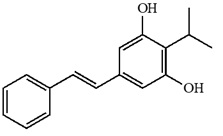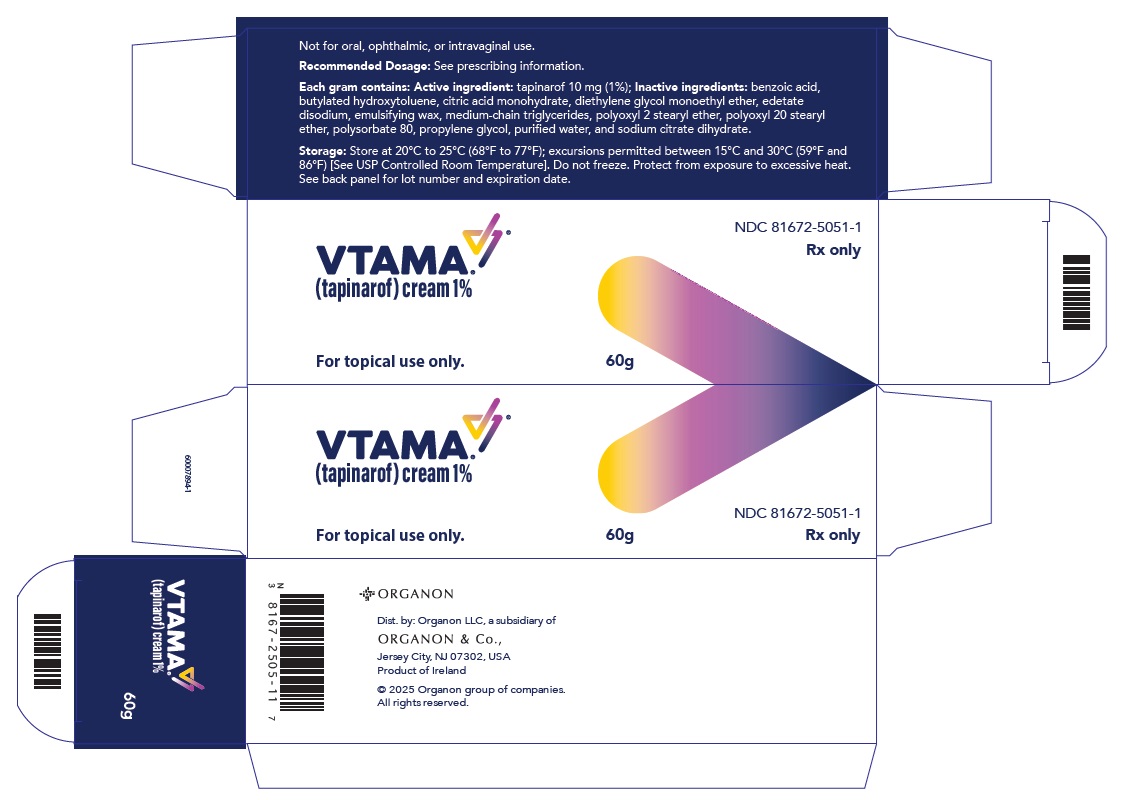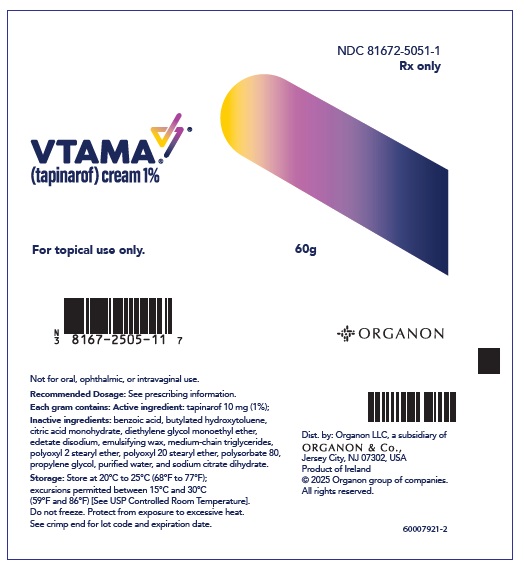 DRUG LABEL: VTAMA
NDC: 81672-5051 | Form: CREAM
Manufacturer: Organon LLC
Category: prescription | Type: HUMAN PRESCRIPTION DRUG LABEL
Date: 20250528

ACTIVE INGREDIENTS: TAPINAROF 10 mg/1 g
INACTIVE INGREDIENTS: BENZOIC ACID; BUTYLATED HYDROXYTOLUENE; CITRIC ACID MONOHYDRATE; DIETHYLENE GLYCOL MONOETHYL ETHER; EDETATE DISODIUM; MEDIUM-CHAIN TRIGLYCERIDES; POLAWAX POLYSORBATE; POLYSORBATE 80; PROPYLENE GLYCOL; STEARETH-2; STEARETH-20; TRISODIUM CITRATE DIHYDRATE; WATER

HIGHLIGHTS OF PRESCRIBING INFORMATION

These highlights do not include all the information needed to use VTAMA® cream safely and effectively. See full prescribing information for VTAMA cream.
VTAMA (tapinarof) cream, for topical use
Initial U.S. Approval: 2022

RECENT MAJOR CHANGES

Indications and Usage (1.2) | 12/2024

1 INDICATIONS AND USAGE

VTAMA cream, 1% is an aryl hydrocarbon receptor agonist indicated for:

- the topical treatment of plaque psoriasis in adults. (1.1)
- the topical treatment of atopic dermatitis in adults and pediatric patients 2 years of age and older. (1.2)

2 DOSAGE AND ADMINISTRATION

- Apply a thin layer of VTAMA cream to affected areas once daily. (2)
- VTAMA cream is not for oral, ophthalmic, or intravaginal use. (2)

3 DOSAGE FORMS AND STRENGTHS

Cream, 1% (3)

Each gram of VTAMA cream contains 10 mg of tapinarof. (3)

4 CONTRAINDICATIONS

None. (4)

6 ADVERSE REACTIONS

- In plaque psoriasis, the most common adverse reactions (incidence ≥ 1%) were folliculitis, nasopharyngitis, contact dermatitis, headache, pruritus, and influenza. (6.1)
- In atopic dermatitis, the most common adverse reactions (incidence ≥ 1%) were upper respiratory tract infection, folliculitis, lower respiratory tract infection, headache, asthma, vomiting, ear infection, pain in extremity, and abdominal pain. (6.1)

To report SUSPECTED ADVERSE REACTIONS, contact Organon LLC, a subsidiary of Organon & Co., at 1-844-674-3200 or FDA at 1-800-FDA-1088 or www.fda.gov/medwatch.

FULL PRESCRIBING INFORMATION

1 INDICATIONS AND USAGE

1.1 Plaque Psoriasis

VTAMA® cream is indicated for the topical treatment of plaque psoriasis in adults.

1.2 Atopic Dermatitis

VTAMA cream is indicated for the topical treatment of atopic dermatitis in adults and pediatric patients 2 years of age and older.

2 DOSAGE AND ADMINISTRATION

Apply a thin layer of VTAMA cream to affected areas once daily.

Wash hands after application, unless VTAMA cream is for treatment of the hands.

VTAMA cream is not for oral, ophthalmic, or intravaginal use.

3 DOSAGE FORMS AND STRENGTHS

Cream, 1%

Each gram of VTAMA cream contains 10 mg of tapinarof in a white to off-white cream.

4 CONTRAINDICATIONS

None.

6 ADVERSE REACTIONS

6.1 Clinical Trials Experience

Because clinical trials are conducted under widely varying conditions, adverse reaction rates observed in the clinical trials of a drug cannot be directly compared to rates in the clinical trials of another drug and may not reflect the rates observed in practice.

Plaque Psoriasis Clinical Trials

In two randomized, double-blind, multicenter, vehicle-controlled clinical trials (PSOARING 1 and PSOARING 2), 1025 adults with plaque psoriasis were treated with VTAMA cream or received vehicle cream once daily for up to 12 weeks.

Subjects ranged in age from 18 to 75 years, with an overall median age of 51 years. The majority of subjects were White (85%) and male (57%); and 85% identified as non-Hispanic or Latino.

Table 1 presents adverse reactions that occurred in at least 1% of subjects treated with VTAMA cream, and for which the rate exceeded the rate for vehicle.

Table 1: Adverse Reactions Occurring in ≥1% of Adult Subjects with Plaque Psoriasis (and More Frequently than Vehicle) in the 12-week PSOARING 1 and PSOARING 2 Clinical Trials
Adverse Reaction | VTAMA cream N=683 n (%) | Vehicle cream N=342 n (%)
Folliculitis [Folliculitis includes application site folliculitis and folliculitis] | 140 (20) | 3 (1)
Nasopharyngitis [Nasopharyngitis includes nasopharyngitis, nasal congestion, pharyngitis, respiratory tract infection (RTI) viral, rhinorrhea, sinus congestion, upper RTI, and viral upper RTI] | 73 (11) | 31 (9)
Contact dermatitis [Contact dermatitis includes dermatitis, contact dermatitis, hand dermatitis, and rash] | 45 (7) | 2 (1)
Headache [Headache includes headache, migraine, and tension headache] | 26 (4) | 5 (1)
Pruritus [Pruritus includes application site pruritus, pruritus, generalized pruritus, and genital pruritus] | 20 (3) | 2 (1)
Influenza [Influenza includes influenza and influenza-like illness] | 14 (2) | 2 (1)

Two (0.3%) subjects using VTAMA cream developed urticaria. Adverse reactions leading to treatment discontinuation in >1% of subjects who received VTAMA cream were contact dermatitis (2.9%) and folliculitis (2.8%).

In an open label safety trial (PSOARING 3), 763 subjects were treated for up to an additional 40 weeks after completing PSOARING 1 or PSOARING 2. In addition to the adverse reactions reported in the 12-week PSOARING 1 and PSOARING 2 clinical trials, the following adverse reactions were reported: urticaria (1.0%) and drug eruption (0.7%).

Atopic Dermatitis Clinical Trials

In two randomized, double-blind, multicenter, vehicle-controlled clinical trials (ADORING 1 and ADORING 2), 811 adult and pediatric subjects 2 years of age and older with atopic dermatitis were treated with VTAMA cream or received vehicle cream once daily for up to 8 weeks.

Subjects ranged in age from 2 to 81 years, with an overall median age of 11 years. The majority (51%) of subjects were White, 31% were Black, 12% were Asian; 54% were female; and 78% of subjects identified as non-Hispanic or Latino.

Table 2 presents adverse reactions that occurred in at least 1% of subjects treated with VTAMA cream, and for which the rate exceeded the rate for vehicle.

Table 2: Adverse Reactions Occurring in ≥1% of Adult and Pediatric Subjects 2 Years and Older with Atopic Dermatitis (and More Frequently than Vehicle) in the 8 week ADORING 1 and ADORING 2 Clinical Trials
Adverse Reaction | VTAMA cream N=541 n (%) | Vehicle cream N=270 n (%)
Upper respiratory tract infection [Upper respiratory tract infection includes upper respiratory tract infection, nasopharyngitis, nasal congestion, sinusitis, pharyngitis streptococcal, cough, oropharyngeal pain, pharyngitis, acute sinusitis, streptococcal infection, streptococcus test positive, viral upper respiratory tract infection, viral infection, rhinorrhea, sinus congestion] | 66 (12) | 15 (6)
Folliculitis [Folliculitis includes folliculitis, application site folliculitis, keratosis pilaris, follicular eczema] | 51 (9) | 3 (1)
Lower respiratory tract infection [Lower respiratory tract infection includes lower respiratory tract infection, COVID-19, influenza, bronchitis, pneumonia] | 25 (5) | 6 (2)
Headache | 23 (4) | 3 (1)
Asthma [Asthma includes asthma, wheezing] | 12 (2) | 1 (0)
Vomiting | 10 (2) | 2 (1)
Ear infection [Ear infection includes ear infection, otitis media, otitis externa, otitis media acute] | 10 (2) | 1 (0)
Pain in extremity [Pain in extremity includes pain in extremity, arthralgia] | 9 (2) | 1 (0)
Abdominal pain [Abdominal pain includes abdominal pain and abdominal pain upper] | 6 (1) | 0 (0)

Application site reactions were reported in 19 (3.5%) subjects treated with VTAMA cream and 9 (3.3%) subjects receiving vehicle.

The adverse reactions observed in pediatric subjects 2 years of age and older were generally consistent with those observed in adults with atopic dermatitis. Adverse reactions occurring more frequently in pediatric subjects compared to adults were upper respiratory tract infection (16.3% in subjects ages 2-6 years of age and 11.2% in subjects ages 7-17 years of age vs. 9.5% in subjects 18 years and older) and ear infection (5.7% in subjects ages 2-6 years of age and 1.4% in subjects ages 7-11 years of age vs. 0% in subjects 12 years and older).

In an open label safety trial (ADORING 3), 728 subjects (124 adult and 604 pediatric subjects 2 years of age and older) were treated for up to 48 weeks. This included 624 subjects completing either ADORING 1 or ADORING 2, 28 subjects completing the maximal usage trial, and 76 subjects treated only in ADORING 3. The safety profile with long term use was generally consistent with the safety profile observed at Week 8.

8 USE IN SPECIFIC POPULATIONS

8.1 Pregnancy

Risk Summary

The available data on VTAMA cream use in pregnant women are insufficient to evaluate for a drug-associated risk of major birth defects, miscarriage, or other adverse maternal or fetal outcomes. In animal reproduction studies, subcutaneous administration of tapinarof to pregnant rats and rabbits during the period of organogenesis resulted in no significant adverse effects at doses 264 and 16 times, respectively, the maximum recommended human dose (MRHD) (see Data).

The estimated background risk of major birth defects and miscarriage for the indicated population is unknown. All pregnancies have a background risk of major birth defects, loss, and other adverse outcomes. In the U.S. general population, the estimated background risk of major birth defects and miscarriage in clinically recognized pregnancies is 2-4% and 15-20%, respectively.

Data

Animal Data

In an embryofetal development study in rats, tapinarof was administered by subcutaneous injection to pregnant animals at doses of 1.2, 6.9 and 34 mg/kg/day during the period of organogenesis. Tapinarof was not associated with embryofetal lethality or fetal malformations. Tapinarof increased the incidence of skeletal variations (incomplete ossification of nasal bones) at the dose of 34 mg/kg/day (264 times the MRHD based on AUC comparisons).

In an embryofetal development study in rabbits, tapinarof was administered by subcutaneous injection to pregnant animals twice daily at doses of 0.3, 1, and 3 mg/kg/day during the period of organogenesis. Maternal toxicity as evidenced by decreased maternal body weight gain and associated increased post-implantation loss (embryolethality) was observed at 3 mg/kg/day. In addition, fetal skeletal variations were observed at 3 mg/kg/day. Tapinarof was not associated with embryofetal lethality or fetal malformations at doses up to 1 mg/kg/day (16 times the MRHD based on AUC comparison) or fetal malformations at doses up to 3 mg/kg/day (30 times the MRHD based on AUC comparison).

In a second embryofetal development study in rabbits, tapinarof was administered by continuous subcutaneous infusion to pregnant animals at doses of 1, 2 and 3 mg/kg/day during the period of organogenesis. Tapinarof was not associated with embryofetal lethality or fetal malformations at doses up to 3 mg/kg/day (20 times the MRHD based on AUC comparison).

In a prenatal and postnatal development study, tapinarof was administered by subcutaneous injection to pregnant rats at doses of 1, 6 and 30 mg/kg/day beginning on gestation day 6 through lactation day 20. Maternal toxicity associated with decreases in body weight gain and food consumption was noted at 30 mg/kg/day (264 times the MRHD based on AUC comparisons). Tapinarof decreased fetal survival and viability that resulted in reduced litter sizes and decreased fetal weights at doses greater than or equal to 6 mg/kg/day (44 times the MRHD based on AUC comparisons). No tapinarof-related effects on fetal survival and viability were noted at a dose of 1 mg/kg/day (6 times the MRHD based on AUC comparisons). No tapinarof-related effects on postnatal development, neurobehavioral or reproductive performance of offspring were noted at doses up to 30 mg/kg/day (264 times the MRHD based on AUC comparison).

8.2 Lactation

Risk Summary

No data are available regarding the presence of tapinarof in human milk or the effects of tapinarof on the breastfed infant, or on milk production. Tapinarof was detected in rat offspring following subcutaneous administration to pregnant female rats which suggests that tapinarof was transferred into the milk of lactating rats (see Data). When a drug is present in animal milk, it is likely that the drug will be present in human milk. The developmental and health benefits of breastfeeding should be considered along with the mother’s clinical need for VTAMA cream and any potential adverse effects on the breastfed infant from VTAMA cream or from the underlying maternal condition.

Data

In a prenatal and postnatal development study, tapinarof was administered by subcutaneous injection to pregnant rats at doses of 1, 6, and 30 mg/kg/day from gestation day 6 through lactation day 20. Tapinarof was quantifiable in offspring plasma samples on postnatal day 10 at doses of 6 and 30 mg/kg/day, suggesting that tapinarof is present in animal milk.

8.4 Pediatric Use

Plaque Psoriasis

The safety and efficacy of VTAMA cream for the topical treatment of plaque psoriasis have not been established in pediatric patients.

Atopic Dermatitis

The safety and efficacy of VTAMA cream for the topical treatment of atopic dermatitis have been established in pediatric patients 2 years of age and older. Use of VTAMA cream for this indication is supported by evidence from two adequate and well-controlled trials (ADORING 1 and ADORING 2), which included 654 pediatric subjects 2 years of age and older (436 of whom received VTAMA cream) with moderate to severe atopic dermatitis. Adverse reactions occurring more frequently in pediatric subjects compared to adults were upper respiratory tract infection and ear infection [see Adverse Reactions (6.1), Clinical Pharmacology (12.3) and Clinical Studies (14.2)].

The safety and efficacy of VTAMA cream for the topical treatment of atopic dermatitis have not been established in pediatric patients younger than 2 years of age.

Juvenile Animal Toxicity Data

In a juvenile animal toxicity study, tapinarof was administered by subcutaneous injection to juvenile rats at doses of 1, 10 and 20 mg/kg/day from postnatal day (PND) 7 to 21 and at doses of 1.5, 15, and 30 mg/kg/day from PND 22 to 77. The dose escalation conducted at PND 22 was implemented to maintain consistent systemic exposure across the duration of the dosing period. Renal pelvic dilatation was observed at doses greater than or equal to 15 mg/kg/day (165 times the MRHD based on AUC comparisons). No adverse effects in juvenile animals were noted at 1.5 mg/kg/day (11 times the MRHD based on AUC comparisons).

8.5 Geriatric Use

Plaque Psoriasis

Of the 683 subjects exposed to VTAMA cream in the PSOARING 1 or PSOARING 2 clinical trials, 99 (14.5%) were 65 years of age and older, including 8 (1.2%) subjects who were 75 years of age and older. No overall differences in efficacy, safety, or tolerability of VTAMA cream were observed between subjects 65 years of age and older and younger adult subjects.

Atopic Dermatitis

Of the 541 subjects exposed to VTAMA cream in the ADORING 1 or ADORING 2 clinical trials, 20 (3.7%) were 65 years of age and older, including 4 (0.7%) subjects who were 75 years of age and older. No overall differences in efficacy, safety, or tolerability were observed between subjects 65 years of age and older and younger adult subjects.

11 DESCRIPTION

VTAMA (tapinarof) cream contains tapinarof as the active ingredient. Tapinarof is an aryl hydrocarbon receptor agonist.

Tapinarof is a white to pale brown powder. Chemically, tapinarof is 3, 5-dihydroxy-4-isopropyl-trans-stilbene, also known as (E)-2-isopropyl-5-styrylbenzene-1,3-diol, with the empirical formula C17H18O2, a molecular weight of 254.32, and the following structural formula.

Each gram of VTAMA cream for topical use contains 10 mg of tapinarof in a white to off-white cream. VTAMA cream also contains the following inactive ingredients: benzoic acid, butylated hydroxytoluene, citric acid monohydrate, diethylene glycol monoethyl ether, edetate disodium, emulsifying wax, medium-chain triglycerides, polyoxyl 2 stearyl ether, polyoxyl 20 stearyl ether, polysorbate 80, propylene glycol, purified water, and sodium citrate dihydrate.

12 CLINICAL PHARMACOLOGY

12.1 Mechanism of Action

Tapinarof is an aryl hydrocarbon receptor (AhR) agonist. The specific mechanisms by which VTAMA cream exerts its therapeutic actions are unknown.

12.2 Pharmacodynamics

Pharmacodynamics of VTAMA cream are unknown.

Cardiac Electrophysiology

At the approved recommended dosage, VTAMA cream does not prolong the QTc interval to any clinically relevant extent.

12.3 Pharmacokinetics

The plasma concentrations of tapinarof were higher in pediatric subjects 2 years of age and older with atopic dermatitis when compared to adult subjects with plaque psoriasis.

Absorption

Adults with Plaque Psoriasis

No accumulation was observed with repeat topical application. Plasma concentration of tapinarof was below the quantifiable limits (BQL) of the assay (lower limit of quantification was 50 pg/mL) in 68% of the PK samples. On Day 1, mean ± SD values of Cmax and AUC0-last were 0.90 ± 1.4 ng/mL and 4.1 ± 6.3 ng.h/mL, respectively, following a mean daily dose of 5.23 g applied to a mean body surface area (BSA) involvement of 27.2% (range 21 to 46%) in 21 subjects with moderate to severe plaque psoriasis. On Day 29, the mean ± SD Cmax and AUC0-last were 0.12 ± 0.15 ng/mL and 0.61 ± 0.65 ng.h/mL, respectively.

Pediatric Subjects with Atopic Dermatitis

The PK of VTAMA cream were investigated in 36 pediatric subjects 2 years of age and older with moderate to severe atopic dermatitis and a mean ± SD BSA involvement of 43% ± 15% (range 26% to 90%). In this study, subjects applied approximately 3.2 g/day for 27 days.

Plasma concentrations were BQL in 25% of PK samples on Day 1 and 76% of PK samples on Day 28. On Day 1, the mean ± SD Cmax and AUC0-last were 2.4 ± 3.9 ng/mL and 4.7 ± 5.6 ng.h/mL, respectively in the overall pediatric population with atopic dermatitis. The mean ± SD Cmax and AUC0-last on Day 1 in pediatric subjects with atopic dermatitis stratified by age is shown in Table 3.

Table 3: Pharmacokinetic Parameters of Tapinarof by Age Group in Pediatric Subjects with Atopic Dermatitis
PK Parameter (Mean ± SD) | 2 – 6 Years | 7 – 11 Years | 12 – 17 Years
Day 1
Cmax (ng/mL) | 3.8 ± 5.87 | 2.2 ± 2.5 | 1.3 ± 1.8
AUC0-t (ng.h/mL) | 5.5 ± 6.2 | 5.2 ± 5.9 | 3.3 ± 4.8
Day 28
Cꚍ (ng/mL) | 0.046 ± 0.107 | 0.089 ± 0.130 | 0.125 ± 0.413
Cꚍ: concentration at the end of 24 h dosing interval on Day 28.

Distribution

Human plasma protein binding of tapinarof is approximately 99% in vitro.

Elimination

Metabolism

Tapinarof is metabolized in the liver by multiple pathways including oxidation, glucuronidation, and sulfation in vitro.

Drug Interaction Studies

In Vitro Studies

Cytochrome P450 (CYP) Enzymes: Tapinarof is not an inhibitor of CYP2B6, CYP2C8, CYP2C9, CYP2C19, CYP2D6 or CYP3A4/5. Tapinarof is not an inducer of CYP1A2, CYP2B6 or CYP3A4.

Transporter Systems: Tapinarof is not an inhibitor of BCRP, MATE1, MATE-2K, OAT1, OAT3, OATP1B1, OATP1B3, OCT1, OCT2, or P-gp. Tapinarof is not a substrate for BCRP, OATP1B1, OATP1B3, or P-gp.

13 NONCLINICAL TOXICOLOGY

13.1 Carcinogenesis, Mutagenesis, Impairment of Fertility

Long-term carcinogenicity studies were conducted in mice (daily topical administration at doses of 0.5, 1.5 and 3% tapinarof cream) and in rats (subcutaneous administration at doses of 0.1, 0.3, and 1 mg/kg/day tapinarof). No drug-related neoplasms were noted in mice after 98 (females) to 102 (males) weeks of daily topical administration at doses up to 3% tapinarof cream (44 times the MRHD based on AUC comparisons). No drug-related neoplasms were noted in female rats after 83 weeks of daily subcutaneous administration at doses up to 1 mg/kg/day tapinarof (9 times the MRHD based on AUC comparisons).

Tapinarof revealed no evidence of mutagenicity or clastogenicity in an Ames assay, an in vitro mammalian chromosomal aberration assay, an in vitro mouse lymphoma assay and two in vivo micronucleus-assays in mice and rats.

Tapinarof did not impair female fertility at subcutaneous doses up to 30 mg/kg/day (264 times the MRHD based on AUC comparisons).

14 CLINICAL STUDIES

14.1 Plaque Psoriasis

Two multicenter, randomized, double-blind, vehicle-controlled trials were conducted to evaluate the safety and efficacy of VTAMA cream for the treatment of adults with plaque psoriasis (PSOARING 1 [NCT03956355] and PSOARING 2 [NCT03983980]). These trials were conducted in a total of 1025 subjects randomized 2:1 to VTAMA cream or vehicle cream applied once daily for 12 weeks to any lesion regardless of anatomic location.

Baseline disease severity was graded using the 5-point Physician’s Global Assessment (PGA). The majority of subjects had “Moderate” disease (82%), while 10% had “Mild” disease, and 8% had “Severe” disease at baseline. The extent of disease involvement assessed by mean body surface area (BSA), excluding the scalp, palms, and soles, was 8% (range 3 to 20%). Subjects ranged in age from 18 to 75 years, with a median age of 51 years. Overall, 57% of the subjects were male and 85% were White.

The primary efficacy endpoint in both studies was the proportion of subjects who achieved treatment success, defined as a PGA score of “Clear” (0) or “Almost Clear” (1) and at least a 2-grade improvement from baseline. Efficacy results from the two trials are summarized in Table 4.

Table 4: Clinical Response at Week 12 in PSOARING 1 and PSOARING 2 in Adults with Plaque Psoriasis (Intent-to-Treat; Multiple Imputation)
Clinical Response | PSOARING 1 |  | PSOARING 2
Clinical Response | VTAMA cream N=340 | Vehicle cream N=170 | VTAMA cream N=343 | Vehicle cream N=172
PGA Treatment Success [Treatment success was defined as a PGA score of “Clear” or “Almost Clear” and at least a 2-grade improvement from baseline.] | 36% | 6% | 40% | 6%
Difference (95% CI) | 29% (22%, 36%) |  | 34% (27%, 41%)

Following 12 weeks of treatment, 73 subjects randomized to VTAMA achieved complete disease clearance (PGA 0) and had VTAMA withdrawn. These subjects were followed for up to 40 additional weeks with a median time to first worsening (PGA ≥ 2 [“Mild”]) of 114 days (95% CI: 85, 142).

14.2 Atopic Dermatitis

Two multicenter, randomized, double-blind, vehicle-controlled trials were conducted to evaluate the safety and efficacy of VTAMA cream for the treatment of adult and pediatric subjects 2 years of age and older with atopic dermatitis (ADORING 1 [NCT05014568] and ADORING 2 [NCT05032859]). These trials were conducted in a total of 813 subjects (80% of subjects were 2 to 17 years of age) randomized 2:1 to VTAMA cream or vehicle cream applied once daily for 8 weeks to any lesion regardless of anatomic location.

Baseline disease severity was graded using the 5-point validated Investigator’s Global Assessment (vIGA-AD™). The majority of subjects had “Moderate” disease (87%), while 13% had “Severe” disease at baseline. The extent of disease involvement assessed by mean affected BSA, excluding the scalp, was 16.8% (range 5 to 44%). The mean baseline Eczema Area and Severity Index (EASI) score was 12.9 (range 4.4 to 36.0). The mean baseline Peak Pruritus Numeric Rating Scale (PP-NRS) score for subjects 12 years of age and older was 6.4 on a scale of 0-10. Subjects ranged in age from 2 to 81 years, with a median age of 11 years. Overall, 54% of the subjects were female, 51% were White, 31% were Black, and 12% were Asian. For ethnicity, 78% of subjects identified as non-Hispanic or Latino.

The primary efficacy endpoint in both trials was the proportion of subjects who achieved treatment success, defined as a vIGA-AD score of “Clear” (0) or “Almost Clear” (1) and at least a 2-grade improvement from baseline. Efficacy was also assessed using a ≥ 4-point improvement in PP-NRS score in subjects 12 years of age and older. Efficacy results from the two trials are summarized in Table 5.

Table 5: Clinical Response at Week 8 in ADORING 1 and ADORING 2 in Adult and Pediatric Subjects with Atopic Dermatitis (Intent-to-Treat; Multiple Imputation)
 | ADORING 1 |  | ADORING 2
 | VTAMA cream | Vehicle cream | VTAMA cream | Vehicle cream
Number of subjects randomized | 270 | 137 | 271 | 135
vIGA-AD Treatment Success [Based on number of subjects randomized.] , [Treatment success was defined as a vIGA-AD score of “Clear” or “Almost Clear” and at least a 2-grade improvement from baseline.] Difference from Vehicle (95% CI) | 45% 32% (23%, 40%) | 14% | 46% 29% (19%, 38%) | 18%
Number of subjects ≥12 years of age with baseline PP-NRS score ≥4 | 103 | 54 | 126 | 64
≥ 4-point improvement in PP-NRS [Based on number of subjects 12 years of age and older whose baseline PP-NRS score was ≥4.] Difference from Vehicle (95% CI) | 56% 22% (5%, 38%) | 34% | 53% 29% (15%, 43%) | 24%

Of the 431 subjects randomized to VTAMA who completed 8 weeks of treatment in ADORING 1 and ADORING 2 and elected to continue follow-up, 51 subjects achieved complete disease clearance (vIGA-AD = 0) and had VTAMA withdrawn. These subjects were followed for up to 48 additional weeks with a median time to first worsening (vIGA-AD ≥ 2 [“Mild”]) of 57 days (95% CI: 30, 79).

16 HOW SUPPLIED/STORAGE AND HANDLING

VTAMA (tapinarof) cream, 1% is a white to off-white cream. Each gram of VTAMA cream contains 10 mg of tapinarof. It is supplied in the following size:

60 g laminated tubes: NDC 81672-5051-1

Storage and Handling:

- Store at 20°C to 25°C (68°F to 77°F) excursions permitted between 15°C and 30°C (59°F and 86°F) [See USP Controlled Room Temperature].
- Do not freeze.
- Protect from exposure to excessive heat.

17 PATIENT COUNSELING INFORMATION

Advise the patient to read the FDA-approved patient labeling (Patient Information).

Administration Instructions [see Dosage and Administration (2)]

- Instruct patients to apply VTAMA cream once daily to affected skin lesions only and avoid unaffected areas of skin.
- Advise patients to wash hands after application unless VTAMA cream is for treatment of the hands.
- Advise patients that VTAMA cream is for external use only.

Dist. by: Organon LLC, a subsidiary of
ORGANON & Co.,
Jersey City, NJ 07302, USA

For patent information: www.organon.com/our-solutions/patent/

vIGA-AD is the trademark of Eli Lilly and Co.

© 2025 Organon group of companies. All rights reserved.

uspi-og0505-cr-2505r000

PATIENT INFORMATION
VTAMA® (Vee-TAM-uh)
(tapinarof)
cream, for topical use

Important information: VTAMA cream is for use on the skin (topical use) only. Do not use VTAMA cream in your eyes, mouth, or vagina.

What is VTAMA cream?
VTAMA cream is a prescription medicine used on the skin (topical) to treat:

- plaque psoriasis in adults.
- atopic dermatitis in adults and children 2 years of age and older.

It is not known if VTAMA cream is safe and effective for the topical treatment of plaque psoriasis in children.
It is not known if VTAMA cream is safe and effective for the topical treatment of atopic dermatitis in children under 2 years of age.

Before using VTAMA cream, tell your healthcare provider about all of your medical conditions, including if you:

- are pregnant or plan to become pregnant. It is not known if VTAMA cream will harm your unborn baby.
- are breastfeeding or plan to breastfeed. It is not known if VTAMA cream passes into your breast milk. Talk to your healthcare provider about the best way to feed your baby during treatment with VTAMA cream.

Tell your healthcare provider about all the medicines you take, including prescription and over-the-counter medicines, vitamins, and herbal supplements.

How should I use VTAMA cream?

- Use VTAMA cream exactly as your healthcare provider tells you to use it.
- Apply a thin layer of VTAMA cream only to the affected skin areas 1 time a day. Avoid applying VTAMA cream to unaffected areas of your skin.
- Wash your hands after applying VTAMA cream unless you are using it to treat your hands.
- If someone else applies VTAMA cream for you, they should wash their hands after application.

What are the possible side effects of VTAMA cream?
The most common side effects of VTAMA cream in people treated for plaque psoriasis include:

- red raised bumps around the hair pores (folliculitis)
- pain or swelling in the nose and throat (nasopharyngitis)
- skin rash or irritation including itching and redness, peeling, burning, or stinging

- headache
- flu

The most common side effects of VTAMA cream in people treated for atopic dermatitis include:

- upper and lower respiratory tract infections
- red raised bumps around the hair pores (folliculitis)
- headache
- asthma

- vomiting
- ear infection
- pain in extremity
- stomach-area (abdominal) pain

VTAMA cream can also cause skin reactions at the treatment site. Tell your healthcare provider if you have itching, irritation, pain, redness, burning or changes in skin color at the treatment site.
These are not all the possible side effects of VTAMA cream.
Call your doctor for medical advice about side effects. You may report side effects to FDA at 1-800-FDA-1088.

How should I store VTAMA cream?

- Store VTAMA cream at room temperature between 68°F to 77°F (20°C to 25°C).
- Do not freeze VTAMA cream.
- Protect VTAMA cream from exposure to excessive heat.

Keep VTAMA cream and all medicines out of the reach of children.

General information about the safe and effective use of VTAMA cream.
Medicines are sometimes prescribed for purposes other than those listed in a Patient Information leaflet. Do not use VTAMA cream for a condition for which it was not prescribed. Do not give VTAMA cream to other people, even if they have the same symptoms that you have. It may harm them. You can ask your pharmacist or healthcare provider for information about VTAMA cream that is written for health professionals.

What are the ingredients in VTAMA cream?
Active ingredient: tapinarof
Inactive ingredients: benzoic acid, butylated hydroxytoluene, citric acid monohydrate, diethylene glycol monoethyl ether, edetate disodium, emulsifying wax, medium-chain triglycerides, polyoxyl 2 stearyl ether, polyoxyl 20 stearyl ether, polysorbate 80, propylene glycol, purified water, and sodium citrate dihydrate.
Dist. by: Organon LLC, a subsidiary of
ORGANON & Co.,
Jersey City, NJ 07302, USA
For patent information: www.organon.com/our-solutions/patent/
© 2025 Organon group of companies. All rights reserved.
usppi-og0505-cr-2505r000
For more information, go to www.VTAMA.com or call 1-844-674-3200.

This Patient Information has been approved by the U.S. Food and Drug Administration.

Revised: 5/2025

PRINCIPAL DISPLAY PANEL

NDC 81672-5051-1

Rx only

VTAMA®
(tapinarof) cream 1%

For topical use only.

60g